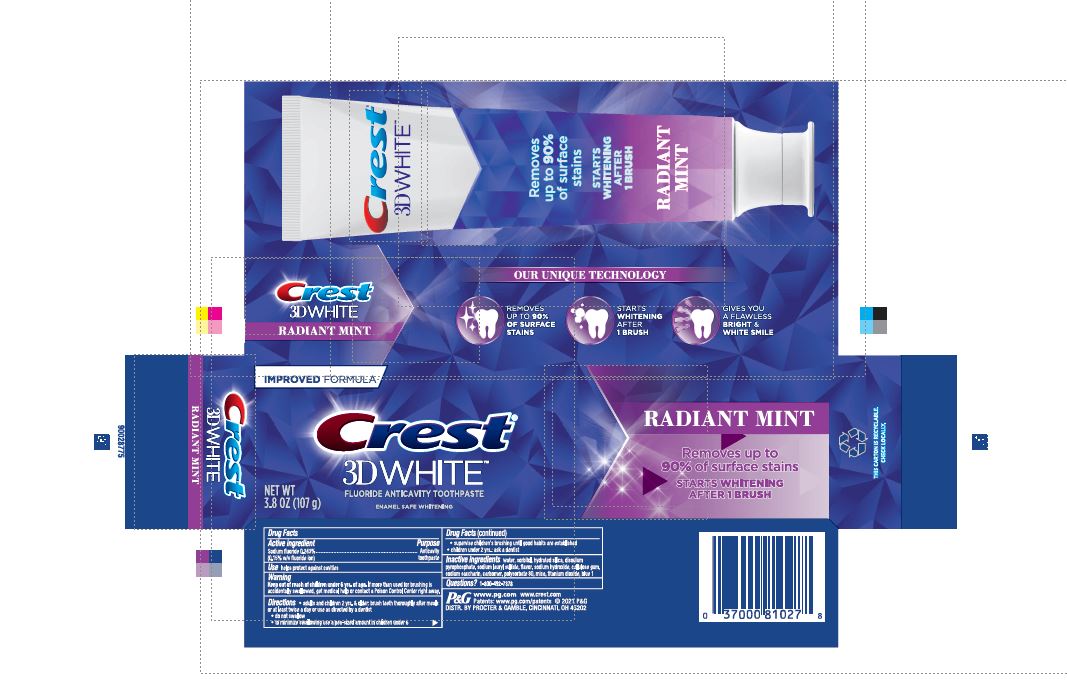 DRUG LABEL: Crest 3D White
NDC: 37000-876 | Form: PASTE, DENTIFRICE
Manufacturer: The Procter & Gamble Manufacturing Company
Category: otc | Type: HUMAN OTC DRUG LABEL
Date: 20251216

ACTIVE INGREDIENTS: SODIUM FLUORIDE 1.5 mg/1 g
INACTIVE INGREDIENTS: WATER; SORBITOL; HYDRATED SILICA; SODIUM ACID PYROPHOSPHATE; SODIUM LAURYL SULFATE; CARBOXYMETHYLCELLULOSE SODIUM, UNSPECIFIED FORM; SODIUM HYDROXIDE; SACCHARIN SODIUM; CARBOXYPOLYMETHYLENE; MICA; TITANIUM DIOXIDE; FD&C BLUE NO. 1; POLYSORBATE 80

Crest® 3D White™
Radiant Mint

Drug Facts

Active ingredient

Sodium fluoride 0.243% (0.15% w/v fluoride ion)

Purpose

Anticavity toothpaste

Use

helps protect against cavities

Warning

Keep out of reach of children under 6 yrs. of age. If more than used for brushing is accidentally swallowed, get medical help or contact a Poison Control Center right away.

Directions

- adults and children 2 yrs. & older: brush teeth thoroughly after meals or at least twice a day or use as directed by a dentist
- do not swallow
- to minimize swallowing use a pea-sized amount in children under 6
  - supervise children's brushing until good habits are established
- children under 2 yrs.: ask a dentist

Inactive ingredients

water, sorbitol, hydrated silica, disodium pyrophosphate, sodium lauryl sulfate, flavor, sodium hydroxide, cellulose gum, sodium saccharin, carbomer, polysorbate 80, mica, titanium dioxide, blue 1

Questions?

1-800-492-7378

DISTR. BY PROCTER & GAMBLE, CINCINNATI, OH 45202

PRINCIPAL DISPLAY PANEL - 85 g Tube Carton

IMPROVED FORMULA

Crest®

3D WHITE™
FLUORIDE ANTICAVITY TOOTHPASTE

ENAMEL SAFE WHITENING

NET WT
3.8 OZ (107 g)

RADIANT MINT

Removes up to 90% of surface stains

STARTS WHITENING AFTER 1 BRUSH